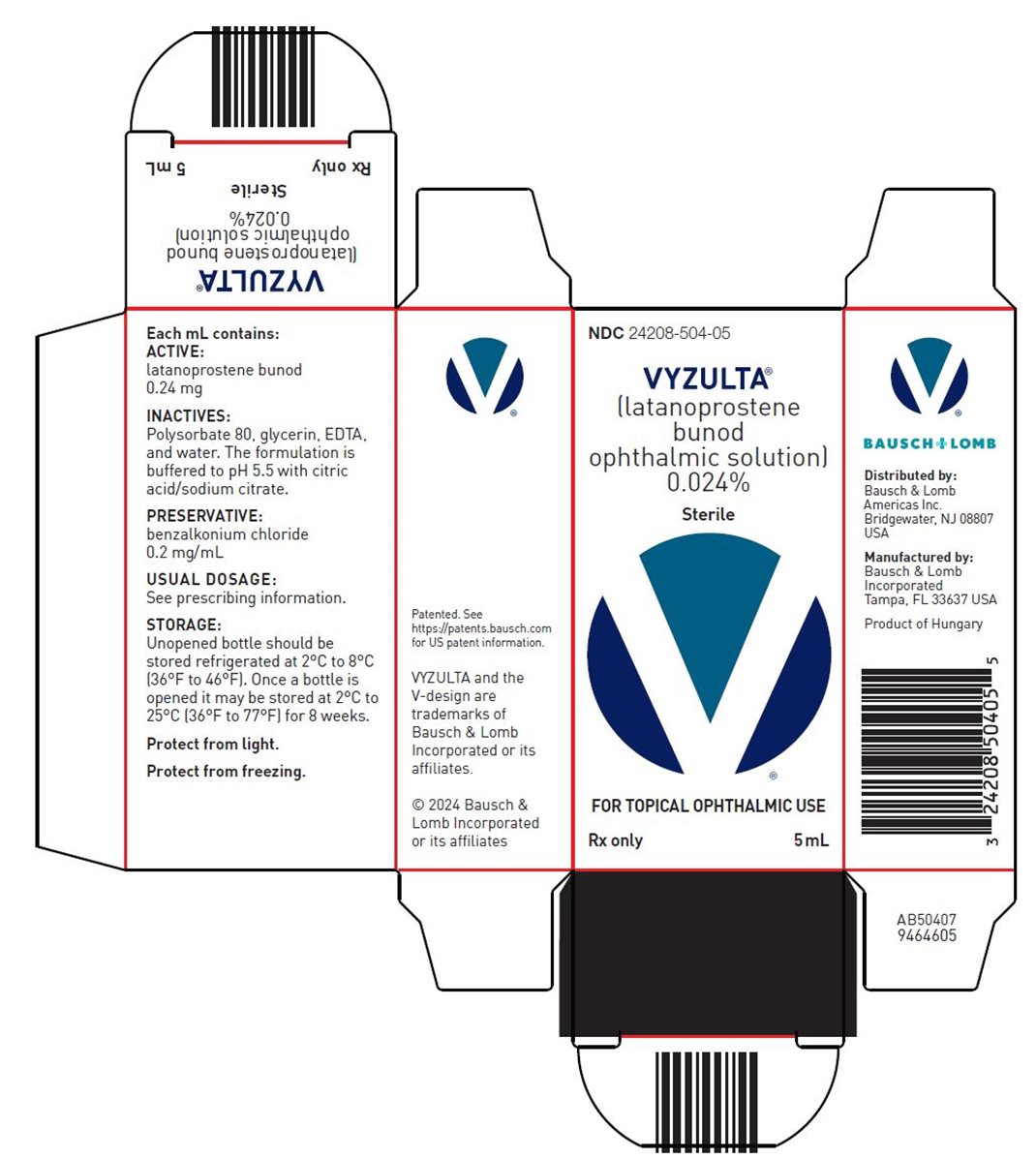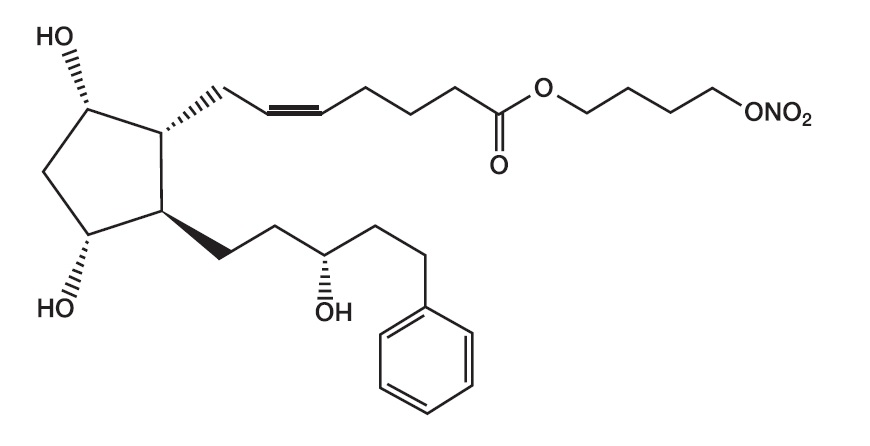 DRUG LABEL: Vyzulta
NDC: 24208-504 | Form: SOLUTION/ DROPS
Manufacturer: Bausch & Lomb Incorporated
Category: prescription | Type: HUMAN PRESCRIPTION DRUG LABEL
Date: 20240227

ACTIVE INGREDIENTS: LATANOPROSTENE BUNOD 0.24 mg/1 mL
INACTIVE INGREDIENTS: BENZALKONIUM CHLORIDE 0.2 mg/1 mL; POLYSORBATE 80; GLYCERIN; EDETATE SODIUM; WATER

HIGHLIGHTS OF PRESCRIBING INFORMATION

These highlights do not include all the information needed to use VYZULTA safely and effectively. See full prescribing information for VYZULTA.
VYZULTA®(latanoprostene bunod ophthalmic solution) 0.024%, for topical ophthalmic use
Initial U.S. Approval: 2017

1 INDICATIONS AND USAGE

VYZULTA is a prostaglandin analog indicated for the reduction of intraocular pressure in patients with open-angle glaucoma or ocular hypertension. (1)

2 DOSAGE AND ADMINISTRATION

One drop in the affected eye(s) once daily in the evening. (2)

3 DOSAGE FORMS AND STRENGTHS

Topical ophthalmic solution: 0.24 mg/mL latanoprostene bunod (0.024%) (3)

4 CONTRAINDICATIONS

None. (4)

5 WARNINGS AND PRECAUTIONS

- Pigmentation: Increased pigmentation of the iris and periorbital tissue (eyelid) can occur. Iris pigmentation is likely to be permanent. (5.1)
- Eyelash changes: Gradual changes to eyelashes including increased length, increased thickness and number of eyelashes. Usually reversible upon discontinuation of treatment. (5.2)

6 ADVERSE REACTIONS

Most common ocular adverse reactions with incidence ≥ 2% are conjunctival hyperemia (6%), eye irritation (4%), eye pain (3%), and instillation site pain (2%). (6.1)

To report SUSPECTED ADVERSE REACTIONS, contact Bausch & Lomb Incorporated at 1-800-553-5340 or FDA at 1-800-FDA-1088 or www.fda.gov/medwatch.

FULL PRESCRIBING INFORMATION

1 INDICATIONS AND USAGE

VYZULTA®(latanoprostene bunod ophthalmic solution) 0.024% is indicated for the reduction of intraocular pressure (IOP) in patients with open-angle glaucoma or ocular hypertension.

2 DOSAGE AND ADMINISTRATION

The recommended dosage is one drop in the conjunctival sac of the affected eye(s) once daily in the evening. Do not administer VYZULTA(latanoprostene bunod ophthalmic solution), 0.024% more than once daily since it has been shown that more frequent administration of prostaglandin analogs may lessen the intraocular pressure lowering effect.

If VYZULTA is to be used concomitantly with other topical ophthalmic drug products to lower intraocular pressure, administer each drug product at least five (5) minutes apart.

3 DOSAGE FORMS AND STRENGTHS

VYZULTA is a topical ophthalmic solution containing latanoprostene bunod, 0.24 mg/mL.

4 CONTRAINDICATIONS

None.

5 WARNINGS AND PRECAUTIONS

5.1 Pigmentation

VYZULTA (latanoprostene bunod ophthalmic solution), 0.024% may cause changes to pigmented tissues. The most frequently reported changes with prostaglandin analogs have been increased pigmentation of the iris and periorbital tissue (eyelid).

Pigmentation is expected to increase as long as latanoprostene bunod ophthalmic solution is administered. The pigmentation change is due to increased melanin content in the melanocytes rather than to an increase in the number of melanocytes. After discontinuation of VYZULTA, pigmentation of the iris is likely to be permanent, while pigmentation of the periorbital tissue and eyelash changes are likely to be reversible in most patients. Patients who receive prostaglandin analogs, including VYZULTA, should be informed of the possibility of increased pigmentation, including permanent changes. The long-term effects of increased pigmentation are not known.

Iris color change may not be noticeable for several months to years. Typically, the brown pigmentation around the pupil spreads concentrically towards the periphery of the iris and the entire iris or parts of the iris become more brownish. Neither nevi nor freckles of the iris appear to be affected by treatment. While treatment with VYZULTA (latanoprostene bunod ophthalmic solution), 0.024% can be continued in patients who develop noticeably increased iris pigmentation, these patients should be examined regularly [see Patient Counseling Information (17)].

5.2 Eyelash Changes

VYZULTA may gradually change eyelashes and vellus hair in the treated eye. These changes include increased length, thickness, and the number of lashes or hairs. Eyelash changes are usually reversible upon discontinuation of treatment.

5.3 Intraocular Inflammation

VYZULTA should be used with caution in patients with a history of intraocular inflammation (iritis/uveitis) and should generally not be used in patients with active intraocular inflammation as it may exacerbate this condition.

5.4 Macular Edema

Macular edema, including cystoid macular edema, has been reported during treatment with prostaglandin analogs. VYZULTA should be used with caution in aphakic patients, in pseudophakic patients with a torn posterior lens capsule, or in patients with known risk factors for macular edema.

5.5 Bacterial Keratitis

There have been reports of bacterial keratitis associated with the use of multiple-dose containers of topical ophthalmic products. These containers had been inadvertently contaminated by patients who, in most cases, had a concurrent corneal disease or a disruption of the ocular epithelial surface.

5.6 Use with Contact Lens

Contact lenses should be removed prior to the administration of VYZULTA because this product contains benzalkonium chloride. Lenses may be reinserted 15 minutes after administration.

6 ADVERSE REACTIONS

The following adverse reactions are described elsewhere in the labeling:

- Pigmentation [see Warnings and Precautions (5.1)]
- Eyelash Changes [see Warnings and Precautions (5.2)]
- Intraocular Inflammation [see Warnings and Precautions (5.3)]
- Macular Edema [see Warnings and Precautions (5.4)]
- Bacterial Keratitis [see Warnings and Precautions (5.5)]
- Use with Contact Lens [see Warnings and Precautions (5.6)]

6.1 Clinical Trials Experience

Because clinical trials are conducted under widely varying conditions, adverse reaction rates observed in the clinical trials of a drug cannot be directly compared to rates in the clinical trials of another drug and may not reflect the rates observed in practice.

VYZULTA was evaluated in 811 patients in 2 controlled clinical trials of up to 12 months duration. The most common ocular adverse reactions observed in patients treated with latanoprostene bunod were: conjunctival hyperemia (6%), eye irritation (4%), eye pain (3%), and instillation site pain (2%). Approximately 0.6% of patients discontinued therapy due to ocular adverse reactions including ocular hyperemia, conjunctival irritation, eye irritation, eye pain, conjunctival edema, vision blurred, punctate keratitis and foreign body sensation.

8 USE IN SPECIFIC POPULATIONS

8.1 Pregnancy

Risk Summary

There are no available human data for the use of VYZULTA during pregnancy to inform any drug associated risks.

Latanoprostene bunod has caused miscarriages, abortion, and fetal harm in rabbits. Latanoprostene bunod was shown to be abortifacient and teratogenic when administered intravenously (IV) to pregnant rabbits at exposures ≥ 0.28 times the clinical dose. Doses ≥ 20 mcg/kg/day (23 times the clinical dose) produced 100% embryofetal lethality. Structural abnormalities observed in rabbit fetuses included anomalies of the great vessels and aortic arch vessels, domed head, sternebral and vertebral skeletal anomalies, limb hyperextension and malrotation, abdominal distension and edema. Latanoprostene bunod was not teratogenic in the rat when administered IV at 150 mcg/kg/day (87 times the clinical dose) [see Data].

The background risk of major birth defects and miscarriage for the indicated population is unknown. However, the background risk in the U.S. general population of major birth defects is 2 to 4%, and of miscarriage is 15 to 20%, of clinically recognized pregnancies.

Data

Animal Data

Embryofetal studies were conducted in pregnant rabbits administered latanoprostene bunod daily by intravenous injection on gestation days 7 through 19, to target the period of organogenesis. The doses administered ranged from 0.24 to 80 mcg/kg/day. Abortion occurred at doses ≥ 0.24 mcg/kg/day latanoprostene bunod (0.28 times the clinical dose, on a body surface area basis, assuming 100% absorption). Embryofetal lethality (resorption) was increased in latanoprostene bunod treatment groups, as evidenced by increases in early resorptions at doses ≥ 0.24 mcg/kg/day and late resorptions at doses ≥ 6 mcg/kg/day (approximately 7 times the clinical dose). No fetuses survived in any rabbit pregnancy at doses of 20 mcg/kg/day (23 times the clinical dose) or greater. Latanoprostene bunod produced structural abnormalities at doses ≥ 0.24 mcg/kg/day (0.28 times the clinical dose). Malformations included anomalies of sternum, coarctation of the aorta with pulmonary trunk dilation, retroesophageal subclavian artery with absent brachiocephalic artery, domed head, forepaw hyperextension and hindlimb malrotation, abdominal distention/edema, and missing/fused caudal vertebrae.

An embryofetal study was conducted in pregnant rats administered latanoprostene bunod daily by intravenous injection on gestation days 7 through 17, to target the period of organogenesis. The doses administered ranged from 150 to 1500 mcg/kg/day. Maternal toxicity was produced at 1500 mcg/kg/day (870 times the clinical dose, on a body surface area basis, assuming 100% absorption), as evidenced by reduced maternal weight gain. Embryofetal lethality (resorption and fetal death) and structural anomalies were produced at doses ≥ 300 mcg/kg/day (174 times the clinical dose). Malformations included anomalies of the sternum, domed head, forepaw hyperextension and hindlimb malrotation, vertebral anomalies and delayed ossification of distal limb bones. A no observed adverse effect level (NOAEL) was established at 150 mcg/kg/day (87 times the clinical dose) in this study.

8.2 Lactation

Risk Summary

There are no data on the presence of VYZULTA in human milk, the effects on the breastfed infant, or the effects on milk production. The developmental and health benefits of breastfeeding should be considered, along with the mother’s clinical need for VYZULTA, and any potential adverse effects on the breastfed infant from VYZULTA.

8.4 Pediatric Use

Use in pediatric patients aged 16 years and younger is not recommended because of potential safety concerns related to increased pigmentation following long-term chronic use.

8.5 Geriatric Use

No overall clinical differences in safety or effectiveness have been observed between elderly and other adult patients.

11 DESCRIPTION

VYZULTA®(latanoprostene bunod ophthalmic solution), 0.024% is a prostaglandin analog formulated as a sterile topical ophthalmic solution. VYZULTA contains the active ingredient latanoprostene bunod 0.24 mg/mL, the preservative benzalkonium chloride 0.2 mg/mL, and the following inactive ingredients: polysorbate 80, glycerin, EDTA, and water. The formulation is buffered to pH 5.5 with citric acid/sodium citrate.

Its chemical name is 4-(Nitrooxy)butyl (5Z)-7-{(1R,2R,3R,5S)-3,5-dihydroxy-2-[(3R)-3-hydroxy-5-phenylpentyl]cyclopentyl}hept-5-enoate. Its molecular formula is C27H41NO8. Molecular weight: 507.62.

Its chemical structure is:

Figure 1

Latanoprostene bunod is a colorless to yellow oil.

12 CLINICAL PHARMACOLOGY

12.1 Mechanism of Action

Latanoprostene bunod is thought to lower intraocular pressure by increasing outflow of aqueous humor through both the trabecular meshwork and uveoscleral routes. Intraocular pressure is a major modifiable risk factor for glaucoma progression. Reduction of intraocular pressure reduces risk of glaucomatous visual field loss.

12.2 Pharmacodynamics

Reduction of the intraocular pressure starts approximately 1 to 3 hours after the first administration with the maximum effect reached after 11-13 hours in eyes with elevated intraocular pressure.

12.3 Pharmacokinetics

Absorption

The systemic exposure of latanoprostene bunod and its metabolites latanoprost acid and butanediol mononitrate were evaluated in one study with 22 healthy subjects after topical ocular administration of VYZULTA 0.024% once daily (one drop bilaterally in the morning) for 28 days. There were no quantifiable plasma concentrations of latanoprostene bunod (lower limit of quantitation, LLOQ, of 10.0 pg/mL) or butanediol mononitrate (LLOQ of 200 pg/mL) post-dose on Day 1 and Day 28. The mean maximal plasma concentrations (Cmax) of latanoprost acid (LLOQ of 30 pg/mL) were 59.1 pg/mL and 51.1 pg/mL on Day 1 and Day 28, respectively. The mean time of maximal plasma concentration (Tmax) for latanoprost acid was approximately 5 minutes post-administration on both Day 1 and Day 28.

Distribution

There were no ocular distribution studies performed in humans.

Metabolism

After topical ocular administration, latanoprostene bunod is rapidly metabolized in the eye to latanoprost acid (active moiety), an F2α prostaglandin analog, and butanediol mononitrate. After latanoprost acid reaches the systemic circulation, it is primarily metabolized by the liver to the 1,2-dinor and 1,2,3,4-tetranor metabolites via fatty acid β-oxidation.

Butanediol mononitrate is metabolized to 1,4-butanediol and nitric oxide. The metabolite 1,4-butanediol is further oxidized to succinic acid and enters the tricarboxylic acid (TCA) cycle.

Elimination

The elimination of latanoprost acid from human plasma is rapid as latanoprost acid plasma concentration dropped below the LLOQ (30 pg/mL) in the majority of subjects by 15 minutes following ocular administration of VYZULTA 0.024% in humans.

13 NONCLINICAL TOXICOLOGY

13.1 Carcinogenesis, Mutagenesis, Impairment of Fertility

Latanoprostene bunod was not mutagenic in bacteria and did not induce micronuclei formation in the in vivorat bone marrow micronucleus assay. Chromosomal aberrations were observed in vitrowith human lymphocytes in the absence of metabolic activation.

Latanoprostene bunod has not been tested for carcinogenic activity in long-term animal studies. Latanoprost acid is a main metabolite of latanoprostene bunod. Exposure of rats and mice to latanoprost acid, resulting from oral dosing with latanoprost in lifetime rodent bioassays, was not carcinogenic.

Fertility studies have not been conducted with latanoprostene bunod. The potential to impact fertility can be partially characterized by exposure to latanoprost acid, a common metabolite of both latanoprostene bunod and latanoprost. Latanoprost acid has not been found to have any effect on male or female fertility in animal studies.

13.2 Animal Toxicology and/or Pharmacology

A 9-month toxicology study administered topical ocular doses of latanoprostene bunod to one eye of cynomolgus monkeys: control (vehicle only), one drop of 0.024% bid, one drop of 0.04% bid and two drops of 0.04% per dose, bid. The systemic exposures are equivalent to 4.2-fold, 7.9-fold, and 13.5-fold the clinical dose, respectively, on a body surface area basis (assuming 100% absorption). Microscopic evaluation of the lungs after 9 months observed pleural/subpleural chronic fibrosis/inflammation in the 0.04% dose male groups, with increasing incidence and severity compared to controls. Lung toxicity was not observed at the 0.024% dose.

14 CLINICAL STUDIES

In clinical studies up to 12 months duration, patients with open-angle glaucoma or ocular hypertension with average baseline intraocular pressures (IOPs) of 26.7 mmHg, the IOP-lowering effect of VYZULTA (latanoprostene bunod ophthalmic solution) 0.024% once daily (in the evening) was up to 7 to 9 mmHg.

16 HOW SUPPLIED/STORAGE AND HANDLING

VYZULTA®(latanoprostene bunod ophthalmic solution), 0.024% is supplied in low density polyethylene bottles with dropper tips and turquoise caps in the following sizes:

2.5 mL fill in a 4 mL white container - NDC 24208-504-02

5 mL fill in a 7.5 mL natural container - NDC 24208-504-05

Storage:Unopened bottle should be stored refrigerated at 2°C to 8°C (36°F to 46°F). Once a bottle is opened it may be stored at 2°C to 25°C (36°F to 77°F) for 8 weeks.

During shipment, bottles may be maintained at temperatures up to 40°C (104°F) for a period not exceeding 14 days.

Protect from light. Protect from freezing.

17 PATIENT COUNSELING INFORMATION

- Potential for Pigmentation
- Patients should be advised about the potential for increased brown pigmentation of the iris, which may be permanent. Patients should also be informed about the possibility of eyelid skin darkening, which is usually reversible after discontinuation of VYZULTA.
- Potential for Eyelash Changes
- Patients should also be informed of the possibility of eyelash and vellus hair changes in the treated eye during treatment with VYZULTA. These changes may result in a disparity between eyes in length, thickness, pigmentation, number of eyelashes or vellus hairs, and/or direction of eyelash growth. Eyelash changes are usually reversible upon discontinuation of treatment.
- Handling the Container
- Patients should be instructed to avoid allowing the tip of the dispensing container to contact the eye, surrounding structures, fingers, or any other surface in order to avoid contamination of the solution by common bacteria known to cause ocular infections. Serious damage to the eye and subsequent loss of vision may result from using contaminated solutions.
- When to Seek Physician Advice
- Advise patients that if they develop a new ocular condition (e.g., trauma or infection), experience a sudden decrease in visual acuity, have ocular surgery, or develop any ocular reactions, particularly conjunctivitis and eyelid reactions, they should immediately seek their physician’s advice concerning the continued use of VYZULTA.
- Use with Contact Lenses
- Contact lenses should be removed prior to administration of the solution. Lenses may be reinserted 15 minutes following administration of VYZULTA.
- Use with Other Ophthalmic Drugs
- If more than one topical ophthalmic drug is being used, the drugs should be administered with at least five (5) minutes between applications.

Patented. See https://patents.bausch.com for US patent information.

VYZULTA is a trademark of Bausch & Lomb Incorporated or its affiliates.

Distributed by:
Bausch & Lomb Americas Inc.
Bridgewater, NJ 08807 USA

Manufactured by:
Bausch & Lomb Incorporated
Tampa, FL 33637 USA

© 2024 Bausch & Lomb Incorporated or its affiliates

9612404 (Folded)
9612304 (Flat)

PACKAGE/LABEL PRINCIPAL DISPLAY PANEL

NDC24208-504-05

VYZULTA®

(latanoprostene

bunod

ophthalmic solution)

0.024%

Sterile

FOR TOPICAL OPHTHALMIC USE

Rx only

5 mL